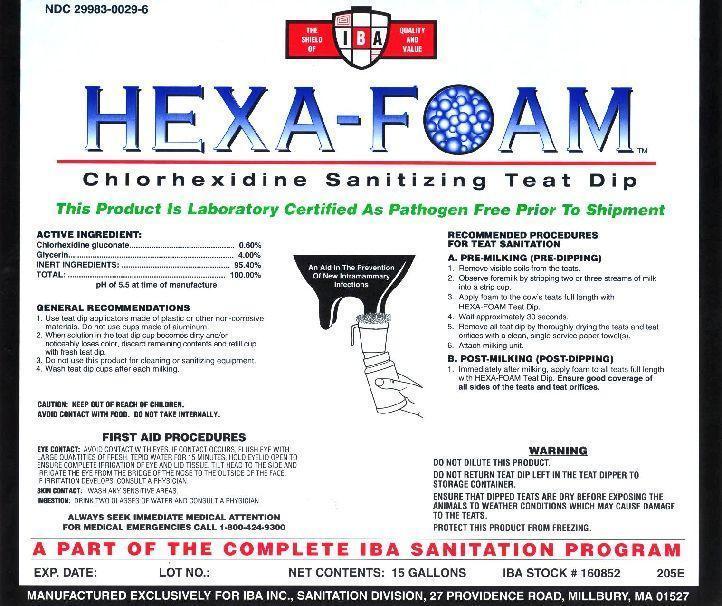 DRUG LABEL: Hexa-Foam
NDC: 29983-0029 | Form: SOLUTION
Manufacturer: IBA
Category: animal | Type: OTC ANIMAL DRUG LABEL
Date: 20220719

ACTIVE INGREDIENTS: CHLORHEXIDINE GLUCONATE 6 g/1 L

HEXA-FOAM CHLOREHEXIDINE SANITIZING TEAT DIP This Product is Laboratory Certified As Pathogen Free Prior to Shipment

ACTIVE INGREDIENT

Chlorhexidine gluconate........................0.60%
INERT INGREDIENTS
Glycerin....................................................4.00%
Other Inerts............................................95.40%
TOTAL:................................................100.00%

pH of 6 at time of manufacture

INDICATIONS AND USAGE

GENERAL RECOMMENDATIONS

1. Use teat dip applicators made of plastic or other non-corrosive materials. Do not use cups made of aluminum.
2. When solution in the teat dip cup becomes dirty and/or noticeably loses color, discard remaining contents and refill cup with fresh teat dip.
3. Do not use this product for cleaning or sanitizing equipment.
4. Wash Teat Dip cups after each milking.

RECOMMENDED PROCEDURES FOR TEAT SANITATION
A. PRE-MILKING (PRE-DIPPING)
1. REMOVE VISIBLE SOILS FROM THE TEATS.
2. OBSERVE FOREMILK BY STRIPPING TWO OR THREE STREAMS OF MILK INTO A STRIP CUP.
3. APPLY FOAM TO THE COW'S TEATS FULL LENGTH WITH HEXA-FOAM TEAT DIP.
4. WAIT APPROXIMATELY 30 SECONDS.
5. REMOVE ALL TEAT DIP BY THOROUGHLY DRYING THE TEATS AND TEAT ORIFICES WITH A CLEAN, SINGLE SERVICE PAPER TOWEL(S).
6. ATTACH MILKING UNIT.
B. POST-MILKING (POST- DIPPING)
Immediately after milking, apply foam to all teats full length with HEXA-FOAM Teat Dip. Ensure good coverage of all sides of the teats and teat orifices.

A PART OF THE COMPLETE IBA SANITATION PROGRAM

WARNING

DO NOT DILUTE THIS PRODUCT.

DO NOT RETURN TEAT DIP LEFT IN THE TEAT DIPPER TO STORAGE CONTAINER
ENSURE THAT DIPPED TEATS ARE DRY BEFORE EXPOSING THE ANIMALS TO WEATHER CONDITIONS WHICH MAY CAUSE DAMAGE TO THE TEATS.

PROTECT THIS PRODUCT FROM FREEZING.

CAUTION: KEEP OUT OF REACH OF CHILDREN.
AVOID CONTACT WITH FOOD. DO NOT TAKE INTERNALLY.

FIRST AID PROCEDURES

EYE CONTACT: IMMEDIATELY FLUSH EYES. IF CONTACT OCCURS, FLUSH EYE WITH LARGE QUANTITIES OF FRESH, TEPID WATER FOR 15 MINUTES. HOLD EYELID OPEN TO ENSURE COMPLETE IRRIGATION OF EYE AND LID TISSUES. TILT HEAD TO THE SIDE AND IRRIGATE THE EYE FROM THE BRIDGE OF THE NOSE TO THE OUTSIDE OF THE FACE. IF IRRITATION DEVELOPS, CONSULT A PHYSICIAN.

SKIN CONTACT: WASH ANY SENSITIVE AREAS.

INGESTION: DRINK TWO GLASSES OF WATER AND CONSULT A PHYSICIAN.

ALWAYS SEEK IMMEDIATE MEDICAL ATTENTION

FOR MEDICAL EMERGENCIES CALL 1-800-424-9300